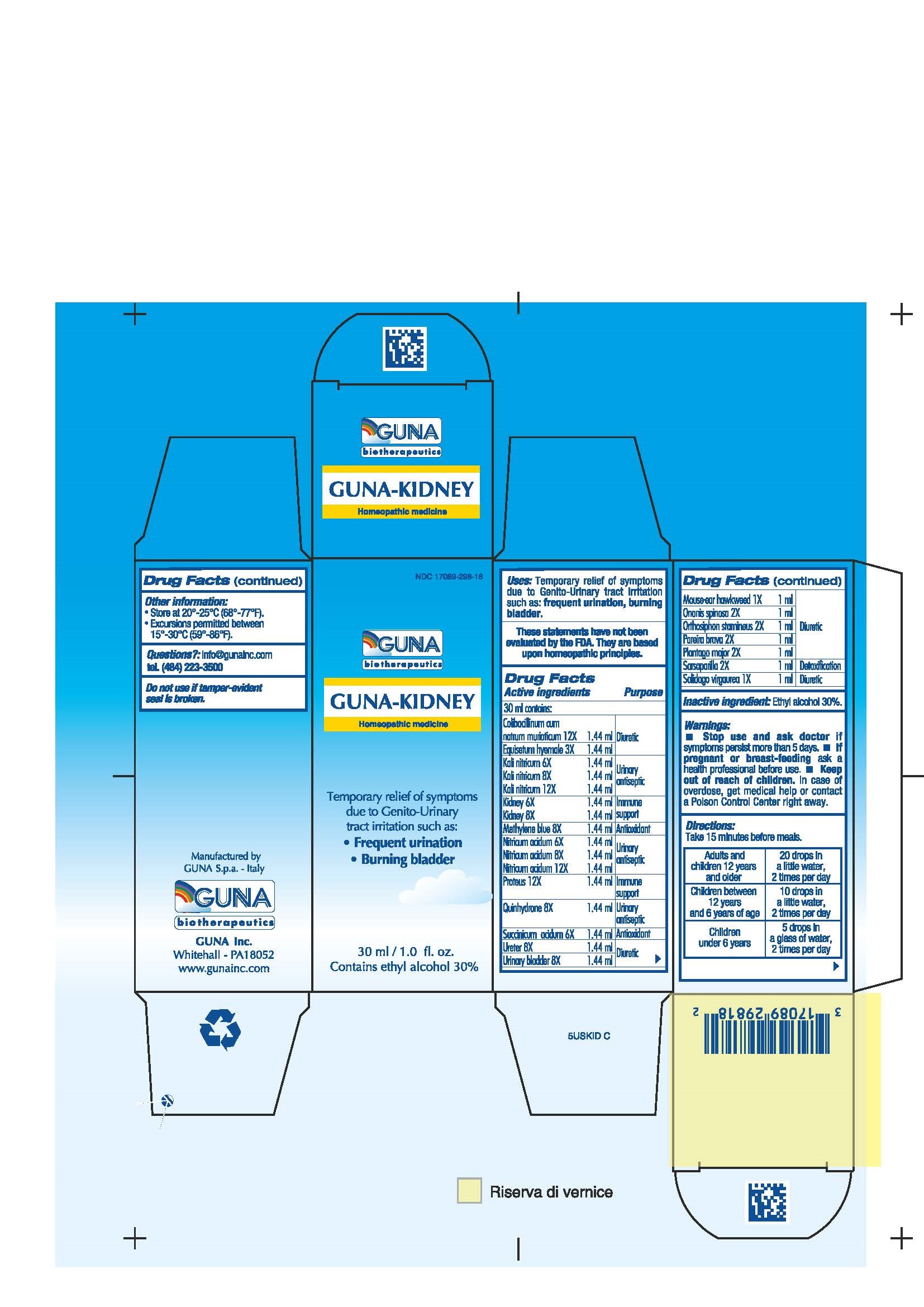 DRUG LABEL: GUNA-KIDNEY
NDC: 17089-298 | Form: SOLUTION/ DROPS
Manufacturer: Guna spa
Category: homeopathic | Type: HUMAN OTC DRUG LABEL
Date: 20221114

ACTIVE INGREDIENTS: ESCHERICHIA COLI 12 [hp_X]/30 mL; EQUISETUM HYEMALE 3 [hp_X]/30 mL; POTASSIUM NITRATE 12 [hp_X]/30 mL; PORK KIDNEY 8 [hp_X]/30 mL; METHYLENE BLUE 8 [hp_X]/30 mL; HIERACIUM PILOSELLA FLOWERING TOP 1 [hp_X]/30 mL; NITRIC ACID 12 [hp_X]/30 mL; ONONIS CAMPESTRIS 2 [hp_X]/30 mL; CLERODENDRANTHUS SPICATUS LEAF 2 [hp_X]/30 mL; CHONDRODENDRON TOMENTOSUM ROOT 2 [hp_X]/30 mL; PLANTAGO MAJOR 2 [hp_X]/30 mL; PROTEUS VULGARIS 12 [hp_X]/30 mL; QUINHYDRONE 8 [hp_X]/30 mL; SARSAPARILLA 2 [hp_X]/30 mL; SOLIDAGO VIRGAUREA FLOWERING TOP 1 [hp_X]/30 mL; SUCCINIC ACID 6 [hp_X]/30 mL; SUS SCROFA URETER 8 [hp_X]/30 mL; SUS SCROFA URINARY BLADDER 8 [hp_X]/30 mL
INACTIVE INGREDIENTS: ALCOHOL 9 mL/30 mL

GUNA-KIDNEY

ACTIVE INGREDIENTS/PURPOSE

COLIBACILLINUM CUM NATRUM MURIATICUM 12 X DIURETIC
EQUISETUM HYEMALE 3 X DIURETIC
KALI NITRICUM 6X 8X 12X URINARY ANTISEPTIC
KIDNEY 6X 8X IMMUNE SUPPORT
METHYLENE BLUE 8X ANTIOXIDANT
MOUSE-EAR HAWKWEED 1X DIURETIC
NITRICUM ACIDUM 6X 8X 12X URINARY ANTISEPTIC
ONONIS SPINOSA 2 X DIURETIC
ORTHOSIPHON STAMINEUS 2 X DIURETIC
PAREIRA BRAVA 2 X DIURETIC
PLANTAGO MAJOR 2 X DIURETIC
PROTEUS 12 X IMMUNE SUPPORT
QUINHYDRONE 8X URINARY ANTISEPTIC
SARSAPARILLA 2 X DETOXIFICATION
SOLIDAGO VIRGAUREA 1 X DIURETIC
SUCCINICUM ACIDUM 6 X ANTIOXIDANT
URETER 8X DIURETIC
URINARY BLADDER 8 X DIURETIC

USES

Temporary relief of symptoms due to Genito-Urinary tract irritation such as:

- Frequent urination
- Burning bladder.

WARNINGS

Stop use and ask doctor if symptoms persist more than 5 days.
If pregnant or breast-feeding ask a health professional before use.
Keep out of reach of children. In case of overdose, get medical help or contact a Poison Control Center right away.
Contains ethyl alcohol 30%

PREGNANCY

If pregnant or breast-feeding ask a doctor before use

WARNINGS

Keep out of reach of children

DIRECTIONS

Adults and children 12 years and older 20 drops in a little water, 2 times per day
Children between 12 years and 6 years of age 10 drops in a little water, 2 times per day
Children under 6 years 5 drops in a glass of water, 2 times per day

QUESTIONS

Questions?: info@gunainc.com, tel. (484) 223-3500

Inactive Ingredient: Ethyl alcohol 30%.

INDICATIONS AND USAGE

Take 15 minutes before meals